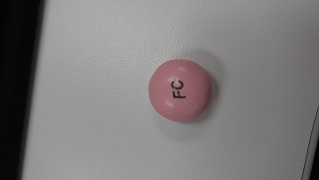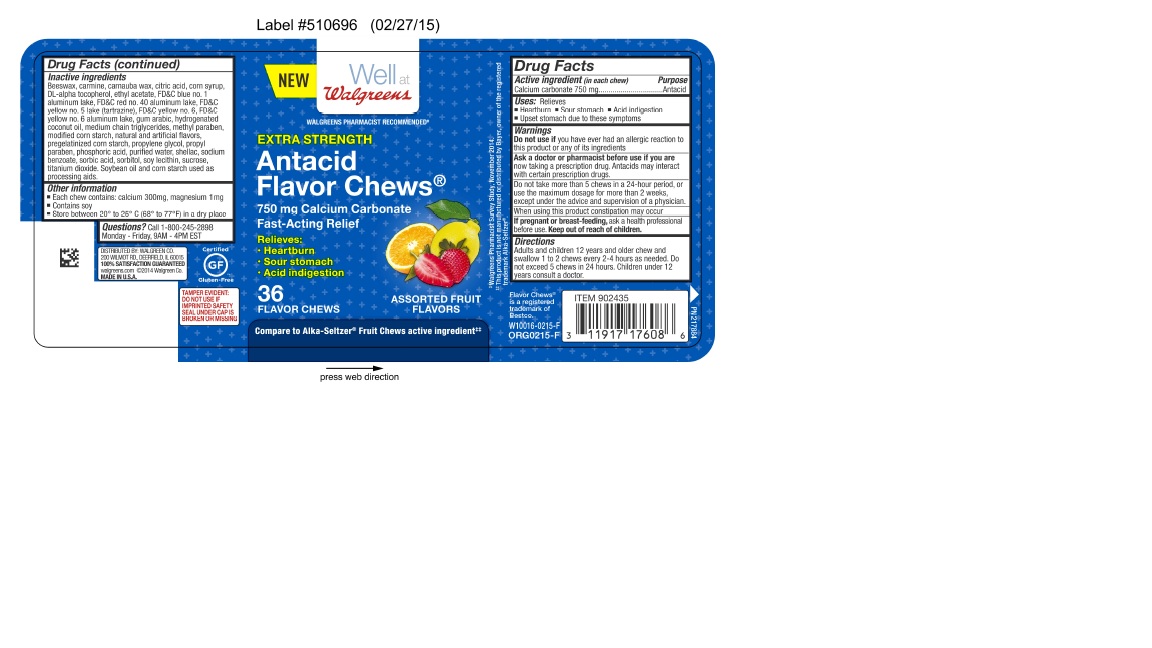 DRUG LABEL: flavor chews
NDC: 0363-0011 | Form: TABLET, CHEWABLE
Manufacturer: Walgreens
Category: otc | Type: HUMAN OTC DRUG LABEL
Date: 20160216

ACTIVE INGREDIENTS: CALCIUM CARBONATE 750 mg/1 1
INACTIVE INGREDIENTS: WATER

calcium carbonate 750 mg

Active Ingredient (in each chew)

Calcium carbonate 750 mg

Purpose

Antacid

Uses:

Relieves

- Heartburn
- Sour stomach
- Acid indigestion
- Upset stomach due to these symptoms

Warnings

Do not use if you have ever had an allergic reaction to this product or any of its ingredients.

Do not take more than 5 chews in a 24 hour period, or use the maxiumum dosage for more than 2 weeks, except under the advice and supervision of a physician.

Ask a doctor or pharmacist before use if you are

now taking a prescription drug. Antacids may interact with certain prescription drugs.

When using this product constipation may occur

PREGNANCY OR BREAST FEEDING

If pregnant or breast-feeding, ask a health professional before use.

Keep out of reach of children

Directions

Adults and children 12 year sand older chew and swallow 1 to 2 chews every 2-4 hours as needed. Do not exceed 5 chews in 24 hours. Children under 12 years consult a doctor.

Inactive ingredients

Beeswax, carmine, carnauba wax, citric acid, corn syrup, DL-alpha tocopherol, ethyl acetate, FD&C blue no. 1 aluminum lake, FD&C red no. 40 aluminum lake, FD&C yellow no. 5 lake (tartrazine), FD&C yellow no. 6, FD&C yellow no. 6 aluminum lake, gum arabic, hydrogenated coconut oil, medium chain triglycerides, methyl paraben, modified corn starch, natural and artificial flavors, pregelatinized corn starch, propylene glycol, propyl paraben, phosphoric acid, purified water, shellac, sodium benzoate, sorbic acid, sorbitol, soy lecithin, sucrose, titanium dioxide. Soybean oil and corn starch are used as processing aids.

Other information

- Each chew contains: calcium 300mg, magnesium 1mg
- Contains soy
- Store between 20 to 25 C (68 to 77 F) in a dry place

Questions?

Call 1-800-245-2898 Monday - Friday 9AM - 4PM EST